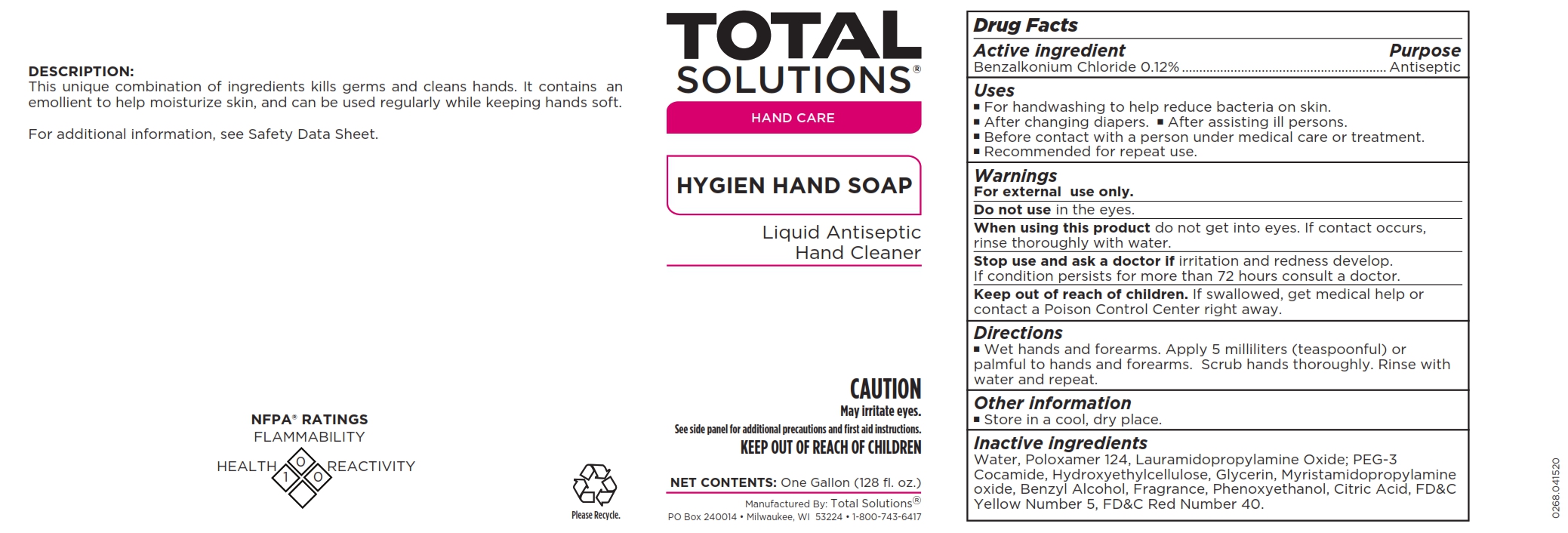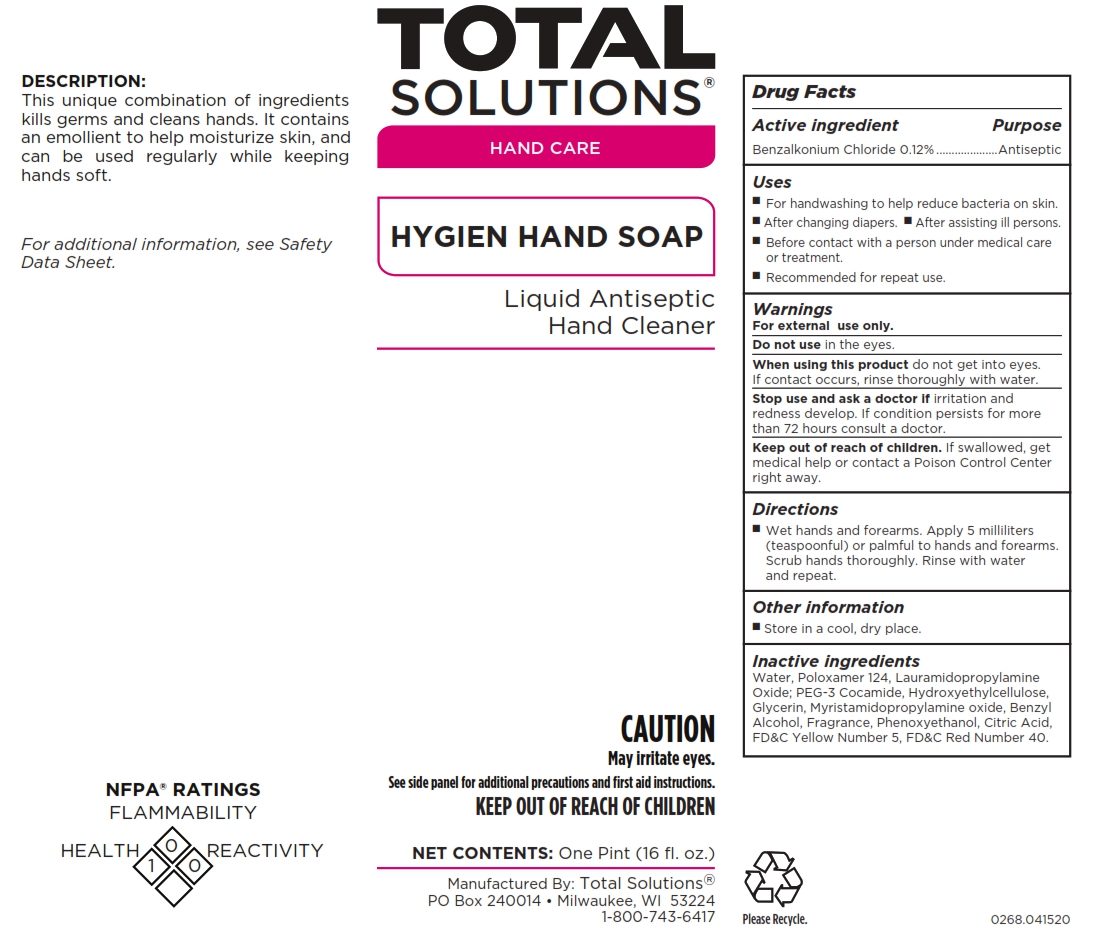 DRUG LABEL: Total Solutions Hygien Hand
NDC: 62819-268 | Form: SOAP
Manufacturer: Athea Laboratories, Inc.
Category: otc | Type: HUMAN OTC DRUG LABEL
Date: 20241230

ACTIVE INGREDIENTS: BENZALKONIUM CHLORIDE 0.12 g/100 mL
INACTIVE INGREDIENTS: WATER 89.26 mL/100 mL; FD&C RED NO. 40 0.0003 g/100 mL; FD&C YELLOW NO. 5 0.0006 g/100 mL; ANHYDROUS CITRIC ACID 0.05 g/100 mL; POLOXAMER 124 4 mL/100 mL; LAURAMIDOPROPYLAMINE OXIDE 2.1 mL/100 mL; MYRISTAMIDOPROPYLAMINE OXIDE 0.7 mL/100 mL; PEG-6 COCAMIDE 1.5 mL/100 mL; HYDROXYETHYL CELLULOSE (5000 CPS AT 1%) 1 mL/100 mL; GLYCERIN 0.8 mL/100 mL; BENZYL ALCOHOL 0.4 mL/100 mL; PHENOXYETHANOL 0.072 mL/100 mL

Total Solutions Hygien Hand Soap

Active ingredient

Benzalkonium Chloride 0.12%

Purpose

Antiseptic

Uses

■ For handwashing to help reduce bacteria on skin. ■ After changing diapers.
■ After assisting ill persons. ■ Before contact with a person under medical care
or treatment. ■ Recommended for repeat use.

Warnings

For external use only

Do not use in the eyes

When using this product do not get into eyes. If contact occurs, rinse thoroughly with
water.

Stop use and ask a doctor if irritation and redness develop. If condition persists for more
than 72 hours consult a doctor.

Keep out of reach of children. If swallowed, get medical help or contact a Poison Control
Center right away.

Directions

■ Wet hands and forearms. Apply 5 milliliters (teaspoonful) or palmful to hands and
forearms. Scrub hands thoroughly. Rinse with water and repeat.

Other information

■ Store in a cool, dry place.

Inactive ingredients

Water, Poloxamer 124, Lauramidopropylamine Oxide; PEG-3 Cocamide, Hydroxyethylcellulose, Glycerin, Myristamidopropylamine oxide, Benzyl Alcohol, Fragrance, Phenoxyethanol, Citric Acid, FD&C Yellow Number 5, FD&C Red Number 40.